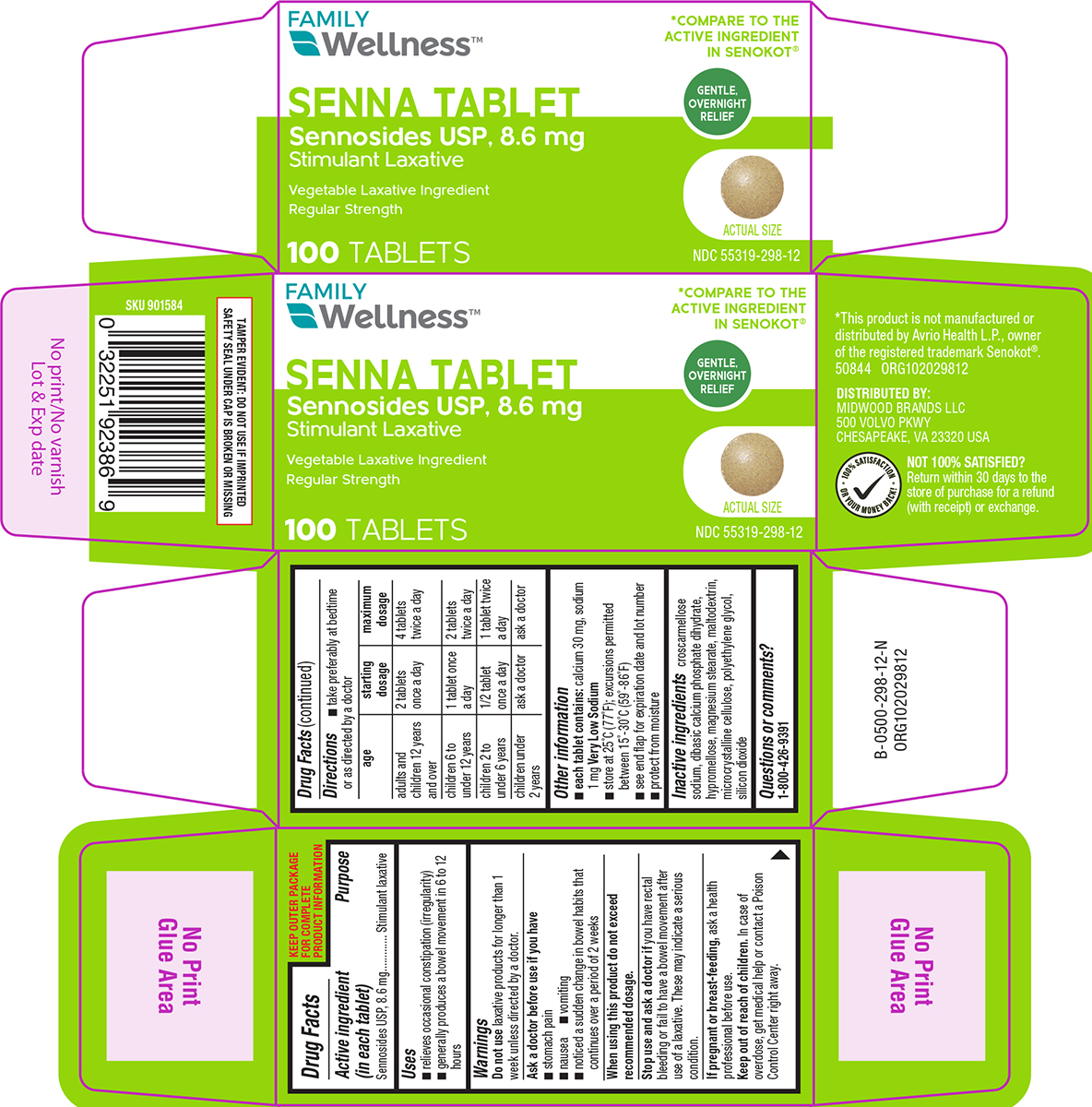 DRUG LABEL: Senna
NDC: 55319-298 | Form: TABLET, FILM COATED
Manufacturer: Family Dollar Services Inc
Category: otc | Type: HUMAN OTC DRUG LABEL
Date: 20251215

ACTIVE INGREDIENTS: SENNOSIDES 8.6 mg/1 1
INACTIVE INGREDIENTS: CROSCARMELLOSE SODIUM; DIBASIC CALCIUM PHOSPHATE DIHYDRATE; HYPROMELLOSE, UNSPECIFIED; MAGNESIUM STEARATE; MALTODEXTRIN; MICROCRYSTALLINE CELLULOSE; POLYETHYLENE GLYCOL, UNSPECIFIED; SILICON DIOXIDE

Family Wellness 44-298

Active ingredient (in each tablet)

Sennosides USP, 8.6 mg

Purpose

Stimulant laxative

Uses

- relieves occasional constipation (irregularity)
- generally produces a bowel movement in 6 to 12 hours

Warnings

Do not use

laxative products for longer than 1 week unless directed by a doctor.

Ask a doctor before use if you have

- stomach pain
- nausea
- vomiting
- noticed a sudden change in bowel habits that continues over a period of 2 weeks

When using this product

do not exceed recommended dosage.

Stop use and ask a doctor if

you have rectal bleeding or fail to have a bowel movement after use of a laxative. These may indicate a serious condition.

If pregnant or breast-feeding,

ask a health professional before use.

Keep out of reach of children.

In case of overdose, get medical help or contact a Poison Control Center right away.

Directions

- take preferably at bedtime or as directed by a doctor

age | starting dosage | maximum dosage
adults and children 12 years and over | 2 tablets once a day | 4 tablets twice a day
children 6 to under 12 years | 1 tablet once a day | 2 tablets twice a day
children 2 to under 6 years | 1/2 tablet once a day | 1 tablet twice a day
children under 2 years | ask a doctor | ask a doctor

Other information

- each tablet contains: calcium 30 mg, sodium 1 mg Very Low Sodium
- store at 25°C (77°F); excursions permitted between 15°-30°C (59°-86°F)
- protect from moisture
- see end flap for expiration date and lot number

Inactive ingredients

croscarmellose sodium, dibasic calcium phosphate dihydrate, hypromellose, magnesium stearate, maltodextrin, microcrystalline cellulose, polyethylene glycol, silicon dioxide

Questions or comments?

1-800-426-9391

Principal Display Panel

FAMILY
Wellness™

*COMPARE TO THE
ACTIVE INGREDIENT
IN SENOKOT®

SENNA TABLET
Sennosides USP, 8.6 mg
Stimulant Laxative

Vegetable Laxative Ingredient
Regular Strength

GENTLE,
OVERNIGHT
RELIEF

ACTUAL SIZE

100 TABLETS

NDC 55319-298-12

TAMPER EVIDENT: DO NOT USE IF IMPRINTED
SAFETY SEAL UNDER CAP IS BROKEN OR MISSING

*This product is not manufactured or
distributed by Avrio Health L.P., owner
of the registered trademark Senokot®.
50844 ORG102029812

DISTRIBUTED BY:
MIDWOOD BRANDS LLC
500 VOLVO PKWY
CHESAPEAKE, VA 23320 USA

NOT 100% SATISFIED?
Return within 30 days to the
store of purchase for a refund
(with receipt) or exchange.

Family Wellness 44-298